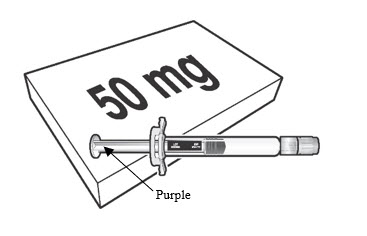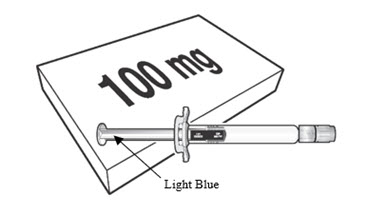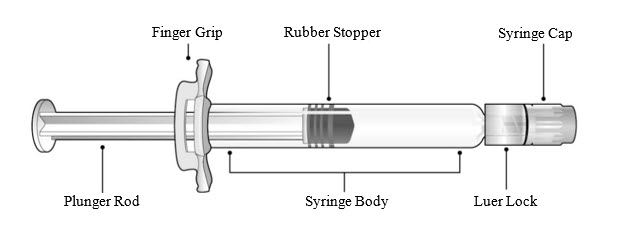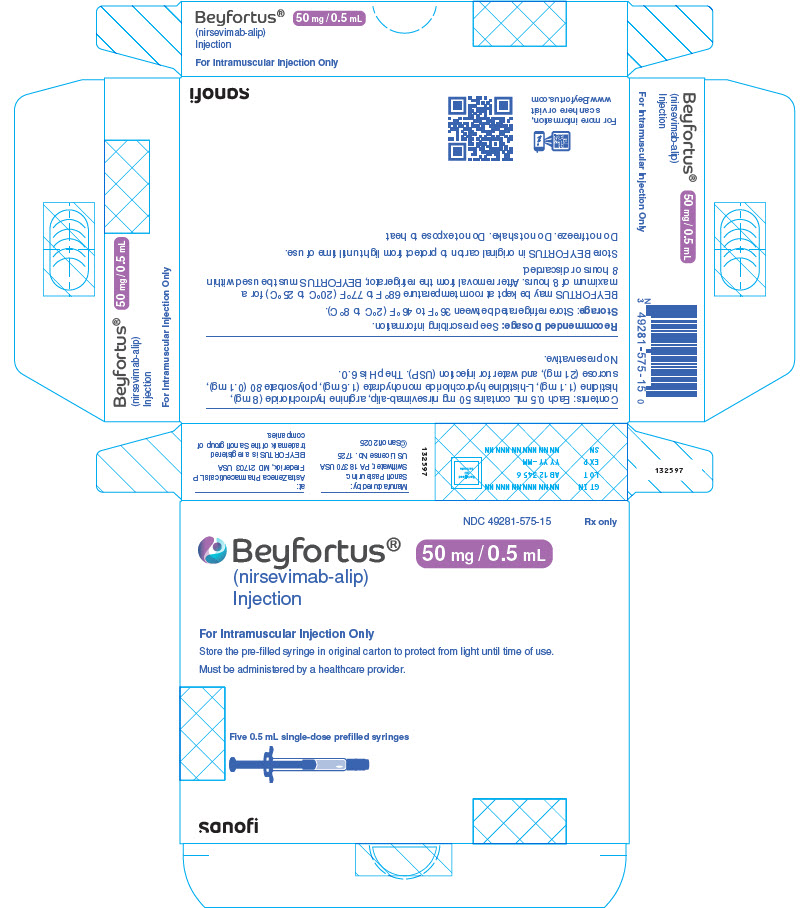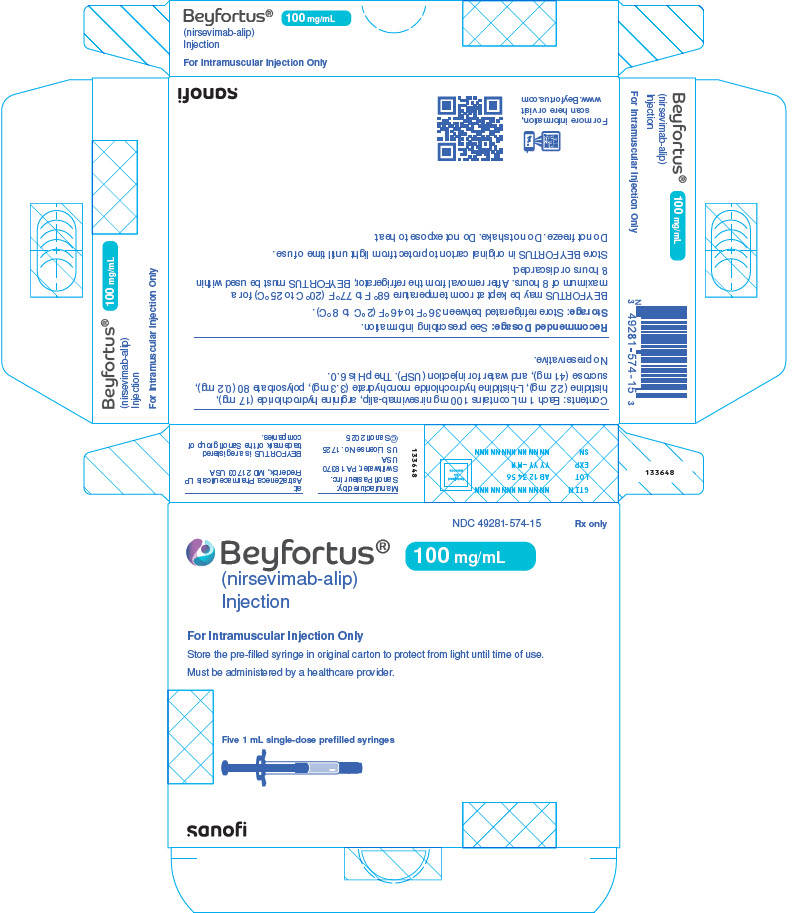 DRUG LABEL: BEYFORTUS
NDC: 49281-575 | Form: INJECTION
Manufacturer: Sanofi Pasteur Inc.
Category: prescription | Type: HUMAN PRESCRIPTION DRUG LABEL
Date: 20260112

ACTIVE INGREDIENTS: NIRSEVIMAB 100 mg/1 mL
INACTIVE INGREDIENTS: HISTIDINE; HISTIDINE HYDROCHLORIDE MONOHYDRATE; ARGININE HYDROCHLORIDE; SUCROSE; POLYSORBATE 80; WATER

HIGHLIGHTS OF PRESCRIBING INFORMATION

These highlights do not include all the information needed to use BEYFORTUS® safely and effectively. See full prescribing information for BEYFORTUS.
BEYFORTUS (nirsevimab-alip) injection, for intramuscular use
Initial U.S. Approval: 2023

1 INDICATIONS AND USAGE

BEYFORTUS is a respiratory syncytial virus (RSV) F protein-directed fusion inhibitor indicated for the prevention of RSV lower respiratory tract disease in:

- Neonates and infants born during or entering their first RSV season. (1)
- Children up to 24 months of age who remain vulnerable to severe RSV disease through their second RSV season. (1)

2 DOSAGE AND ADMINISTRATION

Administer as an intramuscular injection. (2.1)

Recommended dosage:

Neonates and infants born during or entering their first RSV season:

- 50 mg if less than 5 kg in body weight. (2.1)
- 100 mg if greater than or equal to 5 kg in body weight. (2.1)

Children who remain vulnerable through their second RSV season:

- 200 mg (2 × 100 mg injections). (2.1)

3 DOSAGE FORMS AND STRENGTHS

Injection:

- 50 mg/0.5 mL in a single-dose pre-filled syringe. (3)
- 100 mg/mL in a single-dose pre-filled syringe. (3)

4 CONTRAINDICATIONS

BEYFORTUS is contraindicated in infants and children with a history of serious hypersensitivity reactions, including anaphylaxis, to nirsevimab-alip or to any of the excipients. (4)

5 WARNINGS AND PRECAUTIONS

- Hypersensitivity Reactions Including Anaphylaxis: Serious hypersensitivity reactions have been reported following BEYFORTUS administration. These reactions included urticaria, dyspnea, cyanosis, and/or hypotonia. Anaphylaxis has been observed with human immunoglobulin G1 (IgG1) monoclonal antibodies. If signs and symptoms of anaphylaxis or other clinically significant hypersensitivity reactions occur, initiate appropriate treatment. (5.1)

6 ADVERSE REACTIONS

Most common adverse reactions were rash (0.9%) and injection site reactions (0.3%). (6.1)

To report SUSPECTED ADVERSE REACTIONS, contact Sanofi at 1-855-239-3678 or FDA at 1-800-FDA-1088 or www.fda.gov/medwatch.

8 USE IN SPECIFIC POPULATIONS

The safety and effectiveness of BEYFORTUS in children older than 24 months of age have not been established. (8.4)

FULL PRESCRIBING INFORMATION

1 INDICATIONS AND USAGE

BEYFORTUS is indicated for the prevention of Respiratory Syncytial Virus (RSV) lower respiratory tract disease in:

- Neonates and infants born during or entering their first RSV season.
- Children up to 24 months of age who remain vulnerable to severe RSV disease through their second RSV season.

2 DOSAGE AND ADMINISTRATION

2.1 Recommended Dosage

First RSV Season for Neonates and Infants

For neonates and infants born during the RSV season, administer BEYFORTUS starting from birth.
For neonates and infants born outside the RSV season, administer BEYFORTUS once prior to the start of the RSV season considering duration of protection provided by BEYFORTUS [see Clinical Pharmacology (12.2)].

The recommended dosage of BEYFORTUS for neonates and infants born during or entering their first RSV season is based on body weight (see Table 1) and is administered as a single intramuscular (IM) injection.

Table 1 Recommended Dosage of BEYFORTUS for the First RSV Season
Body Weight at Time of Dosing | Recommended Dosage
Less than 5 kg | 50 mg by IM injection
5 kg and greater | 100 mg by IM injection

Second RSV Season for Children Who Remain at Increased Risk for Severe RSV Disease

For children up to 24 months of age, regardless of body weight, who remain at increased risk for severe RSV disease in their second RSV season, refer to Table 2 below for recommended dosage.

Table 2 Recommended Dosage of BEYFORTUS for the Second RSV Season for Children Who Remain at Increased Risk for Severe RSV Disease
Child's Age at Time of Dosing | Recommended Dosage
Up to 24 months of age [Regardless of body weight] | 200 mg administered as two IM injections of (2 × 100 mg)

First and Second RSV Season for Children Undergoing Cardiac Surgery with Cardiopulmonary Bypass

For children undergoing cardiac surgery with cardiopulmonary bypass, an additional dose of BEYFORTUS is recommended as soon as the child is stable after surgery to ensure adequate nirsevimab-alip serum levels. The recommended dosage of BEYFORTUS is administered as an IM injection.

First RSV season:

- If surgery is within 90 days after receiving BEYFORTUS, the additional dose should be based on body weight at the time of the additional dose. Refer to Table 1 for weight-based dosing.
- If more than 90 days have elapsed since receiving BEYFORTUS, the additional dose should be 50 mg regardless of body weight.

Second RSV season:

- If surgery is within 90 days after receiving BEYFORTUS, the additional dose should be 200 mg, regardless of body weight.
- If more than 90 days have elapsed since receiving BEYFORTUS, the additional dose should be 100 mg, regardless of body weight.

2.2 Administration Instructions

BEYFORTUS must be administered by a healthcare provider.

Parenteral drug products should be inspected visually for particulate matter and discoloration prior to administration, whenever solution and container permit. BEYFORTUS is a clear to opalescent, colorless to yellow solution. Do not inject BEYFORTUS if the liquid is cloudy, discolored, or it contains large particles or foreign particulate matter.

Do not use if the BEYFORTUS pre-filled syringe has been dropped or damaged, the security seal on the carton has been broken, or the expiration date has passed.

BEYFORTUS is available in a 50 mg and a 100 mg pre-filled syringe. Check the labels on the BEYFORTUS carton and pre-filled syringe to ensure the correct 50 mg or 100 mg product is being used.

Co-administration with Childhood Vaccines and Immunoglobulin Products

BEYFORTUS can be given concomitantly with childhood vaccines [see Clinical Pharmacology (12.3)]. When administered concomitantly with injectable vaccines, they should be given with separate syringes and at different injection sites. Do not mix BEYFORTUS with any vaccines or medications in the same syringe or vial.

There is no information regarding co-administration of BEYFORTUS with other immunoglobulin products. Palivizumab should not be administered to infants who have already received BEYFORTUS in the same season. There are no data regarding substitution of BEYFORTUS for palivizumab once prophylaxis treatment is initiated with palivizumab for the RSV season. BEYFORTUS may be administered prior to or during the second RSV season to children up to 24 months of age who remain vulnerable to severe RSV disease, and who received palivizumab in their first RSV season [see Adverse Reactions (6.1) and Clinical Studies (14.3)].

Administration Instructions for Single-Dose Pre-filled Syringe

BEYFORTUS 50 mg (50 mg/0.5 mL) pre-filled syringe with a purple plunger rod.

BEYFORTUS 100 mg (100 mg/mL) pre-filled syringe with a light blue plunger rod.

Refer to Figure 1 for pre-filled syringe components.

Figure 1 Luer Lock Syringe Components

Step 1: Holding the Luer lock in one hand (avoid holding the plunger rod or syringe body), unscrew the syringe cap by twisting it counter-clockwise with the other hand.

Step 2: Attach a Luer lock needle to the pre-filled syringe by gently twisting the needle clockwise onto the pre-filled syringe until slight resistance is felt.

Step 3: Hold the syringe body with one hand and carefully pull the needle cover straight off with the other hand. Do not hold the plunger rod while removing the needle cover or the rubber stopper may move. Do not touch the needle or let it touch any surface. Do not recap the needle or detach it from the syringe.

Step 4: Administer the entire contents of the BEYFORTUS pre-filled syringe as an IM injection, preferably in the anterolateral aspect of the thigh. The gluteal muscle should not be used as an injection site because of the risk of damage to the sciatic nerve.

Step 5: Discard syringe into a sharps container.

If two injections are required, repeat Steps 1–5 in a different injection site.

3 DOSAGE FORMS AND STRENGTHS

BEYFORTUS is a clear to opalescent, colorless to yellow solution available as follows:

- Injection: 50 mg/0.5 mL in a single-dose pre-filled syringe.
- Injection: 100 mg/mL in a single-dose pre-filled syringe.

4 CONTRAINDICATIONS

BEYFORTUS is contraindicated in infants and children with a history of serious hypersensitivity reactions, including anaphylaxis, to nirsevimab-alip or to any of the excipients [see Warnings and Precautions (5.1) and Description (11)].

5 WARNINGS AND PRECAUTIONS

5.1 Hypersensitivity Reactions Including Anaphylaxis

Serious hypersensitivity reactions have been reported following BEYFORTUS administration. These reactions included urticaria, dyspnea, cyanosis, and/or hypotonia. Anaphylaxis has been observed with human immunoglobulin G1 (IgG1) monoclonal antibodies. If signs and symptoms of anaphylaxis or other clinically significant hypersensitivity reactions occur, initiate appropriate treatment.

5.2 Use in Individuals with Clinically Significant Bleeding Disorders

As with any other IM injections, BEYFORTUS should be given with caution to infants and children with thrombocytopenia, any coagulation disorder, or to individuals on anticoagulation therapy.

6 ADVERSE REACTIONS

6.1 Clinical Trials Experience

Because clinical trials are conducted under widely varying conditions, adverse reaction rates observed in the clinical trials of a drug cannot be directly compared to rates in the clinical trials of another drug and may not reflect the rates observed in practice.

A total of 3,224 pediatric subjects received the recommended dose of BEYFORTUS in Phase 2 and Phase 3 clinical trials (Trials 03, 04, and 05) including 2,119 infants who were born at 35 weeks gestational age (GA) or older, and 1,105 infants who were born at less than 35 weeks GA. A total of 247 infants of any GA with chronic lung disease (CLD) of prematurity or hemodynamically significant congenital heart disease (CHD) in Trial 05 received the recommended dose of BEYFORTUS.

Neonates and Infants Entering Their First RSV Season (Trial 03 and Trial 04)

Trial 03 was a randomized, double-blind placebo-controlled trial conducted in preterm infants born at a GA of greater than or equal to 29 weeks to less than 35 weeks. Subjects were randomized 2:1 to receive BEYFORTUS (N=968) or placebo (N=479) by IM injection. All subjects randomized to BEYFORTUS received a single 50 mg IM dose regardless of body weight. Safety data in Trial 03 are presented only for the infants in the BEYFORTUS arm who received the recommended dose [infants who weighed less than 5 kg and who received a single dose of 50 mg BEYFORTUS IM (N=572) or placebo (N=288)].

Trial 04 was a Phase 3, randomized, double-blind, placebo-controlled trial conducted in late preterm and term infants born at greater than or equal to 35 weeks GA. Trial 04 enrolled subjects sequentially into two cohorts: the Primary Cohort was used for the primary efficacy analysis [see Clinical Studies (14.3)] and for assessment of safety, and the Safety Cohort was used primarily for safety assessment. All subjects from both cohorts of Trial 04 were included in the safety analysis (BEYFORTUS N=1,997 and placebo N=997). Subjects in Trial 04 weighing less than 5 kg received a single 50 mg IM dose of BEYFORTUS and infants weighing greater than or equal to 5 kg received a single 100 mg IM dose.

Infants who received the recommended dose in Trial 03 and infants in Trial 04 were pooled to evaluate the safety of BEYFORTUS (N=2,570) compared to placebo (N=1,284). At randomization, in this pooled Safety Population from Trials 03 and 04 cohorts, 22% of infants were born at less than 35 weeks GA, 10% of infants were GA greater than or equal to 35 weeks and less than 37 weeks; 68% were GA greater than or equal to 37 weeks; 52% were male; 57% were White; 15% were Black; 4% were American Indian/Alaskan native; 4% were Asian; 1% were Pacific Islander; and 19% were Other or Mixed Race; 30% were Hispanic or Latino; 73% were from Northern Hemisphere; and 53% weighed less than 5 kg. The median age was 2 months; 65% were less than or equal to 3 months; 28% were greater than 3 to less than or equal to 6 months, and 7% were greater than 6 months of age. (Refer to Sections 14.2 and 14.3, Clinical Studies, for a description of the efficacy populations in Trials 03 and 04). In both trials, infants received a single dose of IM BEYFORTUS or placebo on Study Day 1 and were monitored for at least 60 minutes post-dose. Subjects were followed for 360 days post-dose to assess safety. Adverse reactions were reported in 1.2% of subjects who received BEYFORTUS; most (97%) of adverse reactions were mild to moderate in intensity.

Table 3 summarizes the adverse reactions that occurred in Trial 03 and Trial 04 (Safety Population) in subjects who received the recommended dose of BEYFORTUS.

Table 3 Adverse Reactions Reported at an Incidence Higher Than Placebo in the Safety Population [The Safety Population includes all subjects who received the recommended dose of BEYFORTUS in Trials 03 and 04: Primary and Safety cohorts from Trial 04; infants who weighed less than 5 kg and who received the recommended dose of BEYFORTUS (single 50 mg IM dose) in Trial 03.] (Trials 03 and 04)
Adverse Reaction | BEYFORTUS N=2,570 % | Placebo N=1,284 %
Rash [Rash was defined by the following grouped preferred terms: rash, rash macular, rash maculo-papular, rash papular.] (occurring within 14 days post-dose) | 0.9 | 0.6
Injection site reaction [Injection site reaction was defined by the following grouped preferred terms: injection site reaction, injection site pain, injection site induration, injection site edema, injection site swelling.] (occurring within 7 days post-dose) | 0.3 | 0

Infants Born at <35 Weeks Gestational Age and Infants and Children with CLD of Prematurity or Hemodynamically Significant CHD (Trial 05)

RSV Season One

The safety of BEYFORTUS was evaluated in Trial 05, a randomized, double-blind, palivizumab-controlled multicenter trial in infants at high risk for severe RSV disease. These subjects were randomized 2:1 to receive BEYFORTUS (N=614) or palivizumab (N=304) by IM injection. The 614 infants who received BEYFORTUS included 128 preterm infants born at GA less than 29 weeks, 390 preterm infants who were born at 29 weeks or older to less than 35 weeks GA, and 96 late preterm and term infants born at 35 weeks GA or older. Among infants enrolled during their first RSV season, the number of infants with CLD of prematurity or hemodynamically significant CHD were overall 214 and 103, respectively, regardless of gestational age. Of these, 12 infants had both CLD and CHD.

Subjects in Trial 05 weighing less than 5 kg received a single 50 mg IM dose of BEYFORTUS and infants weighing greater than or equal to 5 kg received a single 100 mg IM dose. BEYFORTUS was administered once on Study Day 1 followed by 4 monthly IM doses of placebo; palivizumab was administered IM monthly for 5 months. All subjects were monitored for at least 60 minutes post-dose. Subjects were followed for 360 days post-dose to assess safety.

Adverse reactions reported among Trial 05 subjects who received BEYFORTUS in their first RSV season were similar to those reported in subjects who received BEYFORTUS in Trials 03 and 04.

RSV Season Two (Subjects with CLD of Prematurity and Hemodynamically Significant CHD)

Subjects with CLD of prematurity or hemodynamically significant CHD could continue in Trial 05 and receive BEYFORTUS or palivizumab prior to their second RSV season. All subjects who received BEYFORTUS in the first RSV season also received BEYFORTUS in the second RSV season (N=180). Subjects who received palivizumab in the first RSV season were re-randomized to receive BEYFORTUS (N=40) or palivizumab (N=42) in the second RSV season. Safety data were available for 150 days after dosing in children with CLD or CHD who received BEYFORTUS (N=220) or palivizumab (N=42) in their second RSV season. The safety profile of BEYFORTUS in these children during their second RSV season was consistent with the safety profile of BEYFORTUS observed during their first RSV season.

Term and Preterm Infants Entering Their First RSV Season (Trial 09)

The safety of BEYFORTUS was evaluated in Trial 09, a randomized open-label multicenter trial in 8,034 term and preterm infants (GA greater than or equal to 29 weeks) entering their first RSV season (not eligible for palivizumab), who received BEYFORTUS (N=4,016) or no intervention (N=4,018) for the prevention of RSV LRTI hospitalization. Subjects were followed for 365 days post-dose (BEYFORTUS arm) or post-randomization (no intervention arm) to assess safety. The safety profile of BEYFORTUS administered in the first RSV season was consistent with the safety profile of BEYFORTUS in the placebo-controlled Trials 03 and 04.

6.2 Postmarketing Experience

The following adverse reactions have been identified during post approval use of BEYFORTUS. Because these reactions are reported voluntarily from a population of uncertain size, it is not always possible to reliably estimate their frequency or establish a causal relationship to drug exposure.

Hypersensitivity reactions [see Warnings and Precautions (5.1)].

7 DRUG INTERACTIONS

7.1 Interference with RT-PCR or Rapid Antigen Detection RSV Diagnostic Assays

Nirsevimab-alip does not interfere with reverse transcriptase polymerase chain reaction (RT-PCR) or rapid antigen detection RSV diagnostic assays that employ commercially available antibodies targeting antigenic site I, II, or IV on the RSV fusion (F) protein. For immunological assay results which are negative when clinical observations are consistent with RSV infection, it is recommended to confirm using an RT-PCR-based assay.

8 USE IN SPECIFIC POPULATIONS

8.1 Pregnancy

BEYFORTUS is not indicated for use in females of reproductive potential.

8.2 Lactation

BEYFORTUS is not indicated for use in females of reproductive potential.

8.4 Pediatric Use

The safety and effectiveness of BEYFORTUS have been established for the prevention of RSV lower respiratory tract disease in neonates and infants born during or entering their first RSV season and in children up to 24 months of age who remain vulnerable to severe RSV disease through their second RSV season. The safety and efficacy of BEYFORTUS for this indication and populations are discussed throughout the labeling.

Use of BEYFORTUS for this indication is supported by evidence from adequate and well-controlled studies in neonates and infants from birth up to 12 months of age with additional pharmacokinetic and safety data in children up to 24 months of age [see Adverse Reactions (6.1), Clinical Pharmacology (12.3), and Clinical Studies (14)].

Use of BEYFORTUS in this population is supported by the following:

- Trial 03, a randomized, double-blind, placebo-controlled multicenter trial for the prevention of MA RSV LRTI conducted in preterm infants born at GA greater than or equal to 29 weeks and less than 35 weeks entering their first RSV season;
- Trial 04, a double-blind, placebo-controlled multicenter trial, for the prevention of MA RSV LRTI in term and late preterm infants GA greater than or equal to 35 weeks entering their first RSV season;
- Trial 05, a Phase 2/3 randomized, double-blind, palivizumab-controlled multicenter trial in pediatric subjects born less than 35 weeks GA and infants with CLD of prematurity or hemodynamically significant CHD entering their first or second RSV season.

In addition, BEYFORTUS was evaluated in an open-label, uncontrolled, single-dose trial (Trial 08) in 100 infants and children who were less than or equal to 24 months of age, who received BEYFORTUS in their first or second RSV season, and who had a wide variety of underlying diseases or treatments resulting in immune compromise. The safety profile of BEYFORTUS administered in Trial 08 was consistent with the safety profile of other trials of BEYFORTUS in infants and children [see Clinical Pharmacology (12.3)].

Trial 09 is a Phase 3b randomized, open-label trial of BEYFORTUS compared to no intervention for the prevention of hospitalization in term and preterm infants (GA greater than or equal to 29 weeks) born during or entering their first RSV season [see Adverse Reactions (6.1) and Clinical Studies (14.5)].

The safety and effectiveness of BEYFORTUS have not been established in children older than 24 months of age.

10 OVERDOSAGE

There is limited experience of overdose with BEYFORTUS.

There is no specific treatment for an overdose with BEYFORTUS. In the event of an overdose, the individual should be monitored for the occurrence of adverse reactions and provided with symptomatic treatment as appropriate.

11 DESCRIPTION

Nirsevimab-alip, a respiratory syncytial virus F protein-directed fusion inhibitor, is a human immunoglobulin G1 kappa (IgG1κ) monoclonal antibody produced in Chinese hamster ovary (CHO) cells by recombinant DNA technology. The molecular weight is approximately 146.3 kDa.

BEYFORTUS (nirsevimab-alip) injection is a sterile, preservative-free, clear to opalescent, colorless to yellow solution for intramuscular injection. It is supplied in a single-dose siliconized Luer lock Type I glass pre-filled syringe with a FluroTec coated plunger stopper.

Each 0.5 mL contains 50 mg nirsevimab-alip, arginine hydrochloride (8 mg), histidine (1.1 mg), L-histidine hydrochloride monohydrate (1.6 mg), polysorbate 80 (0.1 mg), sucrose (21 mg), and water for injection (USP). The pH is 6.0.

Each 1 mL contains 100 mg nirsevimab-alip, arginine hydrochloride (17 mg), histidine (2.2 mg), L-histidine hydrochloride monohydrate (3.3 mg), polysorbate 80 (0.2 mg), sucrose (41 mg), and water for injection (USP). The pH is 6.0.

12 CLINICAL PHARMACOLOGY

12.1 Mechanism of Action

BEYFORTUS is a monoclonal antibody with anti-RSV activity [see Microbiology (12.4)].

12.2 Pharmacodynamics

There is a positive correlation between a serum nirsevimab-alip AUC (based on clearance at baseline) above 12.8 mg*day/mL and a lower incidence of medically attended RSV lower respiratory tract infection (MA RSV LRTI). Following IM administration of nirsevimab-alip in adults, RSV neutralizing antibody levels in serum were approximately 4 times higher than baseline at 8 hours after nirsevimab-alip dosing, and maximum levels were reached by day 6 following IM administration of nirsevimab-alip in adults. The safety and effectiveness of BEYFORTUS have not been established in adults.

Duration of Protection

Based on clinical data, the duration of protection offered by a single dose of BEYFORTUS extends through 5 months.

12.3 Pharmacokinetics

The PK of nirsevimab-alip is dose-proportional following a single IM administration of doses ranging from 25 mg (0.5 times the lowest approved recommended dosage) to 200 mg in pediatric subjects. Following the recommended dose, the nirsevimab-alip serum exposures were similar in neonates and infants born during or entering their first RSV season (Trials 03 and 04), and in neonates and infants born at less than 35 weeks GA (including less than 29 weeks GA) in their first RSV season (Trial 05), and in pediatric subjects up to 24 months of age with CLD or CHD in their first and second RSV season (Trial 05).

Absorption

The estimated nirsevimab-alip absolute bioavailability is 84% and the median time (range) to maximum concentration is 6 (1, 28) days.

Distribution

The estimated nirsevimab-alip total volume of distribution is 477 mL, for an infant weighing 5 kg.

Elimination

The nirsevimab-alip terminal half-life is approximately 71 days and the estimated clearance is 3.42 mL/day for an infant weighing 5 kg.

Metabolism

Nirsevimab-alip is degraded into small peptides by catabolic pathways.

Specific Populations

No clinically significant differences in the pharmacokinetics of nirsevimab-alip were observed based on race or vulnerability to severe RSV disease (i.e., CLD, CHD, GA <29 weeks).

The mean and median serum nirsevimab-alip concentrations in Trial 08 were lower than the concentrations in Trials 04 and 05. However, Trial 08 exposures were within the range shown to be effective in those who received the recommended dosage in Trials 03, 04, and 05 [see Pediatric Use (8.4)].

Drug Interaction Studies

No formal drug interaction studies have been performed with BEYFORTUS. Nirsevimab-alip is not predicted to be a substrate of, inhibitor or inducer of cytochrome P450 enzymes or transporter systems based on a mechanistic understanding of monoclonal antibodies.

Clinical Studies

Vaccines: There is limited experience with co-administration of BEYFORTUS with vaccines. In clinical trials, when BEYFORTUS was given concomitantly with routine childhood vaccines, the safety and reactogenicity profile of the co-administered regimen was similar to the childhood vaccines given alone.

12.4 Microbiology

Mechanism of Action

Nirsevimab-alip is a recombinant human IgG1κ monoclonal antibody that provides passive immunity by targeting the prefusion conformation of the RSV F protein. Nirsevimab-alip is long-acting due to a triple amino acid substitution (YTE) in the Fc region which increases binding to the neonatal Fc receptor and thereby extends serum half-life. Nirsevimab-alip binds to a conserved epitope in antigenic site Ø on the prefusion protein with dissociation constants KD = 0.12 nM and KD = 1.22 nM for RSV subtype A and B strains, respectively; it neutralizes RSV by inhibiting conformation changes in the F protein necessary for fusion of the viral and cellular membranes and viral entry.

Antiviral Activity

The cell culture neutralization activity of nirsevimab-alip against RSV was measured in a concentration-response model using cultured Hep-2 cells. Nirsevimab-alip neutralized clinical RSV isolates collected from global locations between 2003 and 2017 with median EC50 values for RSV A of 21 pM (3.2 ng/mL) (n=70; range 3 pM [0.48 ng/mL] to 100 pM [15 ng/mL]) and for RSV B of 19 pM (2.9 ng/mL) (n=49; range 2 pM [0.3 ng/mL] to 398 pM [59.7 ng/mL]).

Antiviral Resistance

In Cell Culture

Escape variants were selected following three passages in cell culture of RSV A2 and B9320 strains in the presence of nirsevimab-alip. Recombinant RSV A variants that showed reduced susceptibility to nirsevimab-alip compared with the reference strain included those with substitutions N67I+N208Y (103-fold reduction). Recombinant RSV B variants that showed reduced susceptibility to nirsevimab-alip included those with substitutions N208D (>90,000-fold change), N208S (>24,000-fold change), K68N+N201S (>13,000-fold change), and K68N+N208S (>90,000-fold change). All resistance-associated substitutions identified among neutralization escape variants were located in the nirsevimab-alip binding site (amino acids 62–69 and 196–212) and were shown to reduce binding affinity to RSV F protein.

In Surveillance Trials

Polymorphisms conferring large fold-reductions in susceptibility to nirsevimab-alip in isolates collected from 1956–2014 were not observed for RSV A and seen rarely (<1%) for RSV B, and included K65Q+K68N (1,239-fold change), K65Q+S211N (36-fold change), and L203I (3,005-fold change) substitutions. In prospective, observational, global molecular epidemiology studies (OUTSMART-RSV and INFORM-RSV) genetic diversity of RSV F protein sequences has remained low (most amino acids in both RSV A and RSV B >99% conserved). Variants harboring known nirsevimab-alip resistance-associated substitutions have been rare (<1%) and include RSV B substitutions K68Q (>369-fold change), N201T (>406-fold change) and N201T+I206M+Q209R (>418-fold change). Variants observed with reduced susceptibility include RSV A substitutions K68E (13-fold change), K68N (5-fold change), and S275F (6-fold change), and RSV B substitutions K68N (30-fold change), K68Q+I206M+Q209R (46-fold change), N201S (127-fold change) and N201S+I206M+Q209R (17-fold change). The clinical significance of these reductions in susceptibility is not known. From 2015 to 2021, most amino acid residues in the nirsevimab-alip binding site were highly conserved (>99%) at all positions in RSV A and 22 of the 25 positions in RSV B. Co-occurring substitutions I206M+Q209R in the nirsevimab-alip binding site that have become prevalent in RSV B since 2017 did not confer reduced susceptibility (<5-fold change) to nirsevimab-alip. The S211N substitution which has increased in prevalence also retains susceptibility to nirsevimab-alip, both individually and concurrently with I206M+Q209R.

In Clinical Trials

In Trial 04, Trial 05 and Trial 08 no known resistance-associated substitutions were identified at ≥25% frequency at any sampling time points. Phenotypic testing of novel substitutions is ongoing.

In Trial 03 (who received a single dose of 50 mg BEYFORTUS), 2 of 40 subjects with RSV infections corresponding to any case definition had a variant containing nirsevimab-alip resistance-associated substitutions. The two subjects received less than the recommended nirsevimab-alip dose and had RSV B variants harboring I64T+K68E+I206M+Q209R co-occurring substitutions or an N208S substitution. I64T, K68E, and N208S substitutions individually have reduced susceptibility to nirsevimab-alip (fold changes: >496, >283, and >387, respectively).

In Trial 04, an RSV B variant harboring binding site substitution L204S (no phenotypic data) concurrent with I206M+Q209R+S211N substitutions (<5-fold change) was detected at ≥25% frequency in one subject who received BEYFORTUS through Day 150. RSV B variants present at <25% frequency with I64T+K68E substitutions (>280-fold-change) and N208I substitution (>600-fold change) were seen in one subject each who received BEYFORTUS through Day 150 and an RSV B N201D substitution (>613-fold change) was observed in one subject after Day 150. In addition, an RSV A K209E substitution (135-fold change) was observed at <25% frequency in one subject after Day 150.

Cross-resistance

Limited data are available that show that variants resistant to nirsevimab-alip could have cross-resistance to palivizumab. Palivizumab retained full neutralization potency against resistance-associated substitutions identified in Trial 03 and Trial 04. Nirsevimab-alip retained activity against recombinant RSV harboring palivizumab resistance-associated substitutions identified in molecular epidemiology studies and in neutralization escape variants of palivizumab; S275F substitution had reduced susceptibility of 6-fold.

12.6 Immunogenicity

The observed incidence of anti-drug antibodies (ADA) is highly dependent on the sensitivity and specificity of the assay. Differences in assay methods preclude meaningful comparisons of the incidence of ADA in the studies described below with the incidence of ADA in other studies, including those of nirsevimab-alip or of other nirsevimab products.

Of 572 subjects receiving the recommended dose of nirsevimab-alip in Trial 03, 3.3% (16/492) subjects were ADA-positive on Day 361. Among the 16 ADA-positive subjects, 94% (15/16) had ADA against YTE and none tested positive for neutralizing antibodies against nirsevimab-alip.

In Trial 04, 5% (95/1778) of subjects were ADA-positive on Day 361, of whom 21% (20/95) had neutralizing antibodies and 77% (73/95) had ADA against YTE.

In Trial 05, among subjects enrolled during their first RSV season, on Day 361, 6% (32/538) of subjects were positive for ADA. Among the 32 ADA-positive subjects, 6% (2/32) had neutralizing antibodies against nirsevimab-alip and 91% (29/32) had antibodies against the YTE substitution. Of 180 subjects who received nirsevimab-alip in two consecutive RSV seasons, on season 2 Day 361, 9% (13/144) of subjects were positive for ADA. Among the 13 ADA-positive subjects, 8% (1/13) had neutralizing antibodies against nirsevimab-alip and 62% (8/13) had antibodies against YTE.

In Trial 08, among subjects receiving nirsevimab-alip in their first or second RSV season, 13% (9/67) of subjects were positive for ADA on Day 361. Among the 9 ADA-positive subjects, 11% (1/9) had neutralizing antibodies against nirsevimab-alip and 100% (9/9) were positive for ADA against YTE.

In Trials 03, 04, 05, and 08 the effect of ADA on nirsevimab-alip serum concentrations through Day 151 could not be determined. Subjects who received BEYFORTUS who developed anti-nirsevimab-alip antibodies had reduced nirsevimab-alip concentrations at Day 361 (40% to 60% lower compared to subjects who received BEYFORTUS who did not develop anti-nirsevimab-alip antibodies). Because of the low occurrence of ADA and MA RSV LRTI in clinical trials, the effect of these ADA on effectiveness of BEYFORTUS is unknown.

13 NONCLINICAL TOXICOLOGY

13.1 Carcinogenesis, Mutagenesis, Impairment of Fertility

Carcinogenesis, mutagenesis and reproductive toxicity studies have not been performed with BEYFORTUS.

14 CLINICAL STUDIES

14.1 Description of Clinical Trials

The efficacy and safety of BEYFORTUS were evaluated in term and preterm infants and children in the trials summarized in Table 4.

Table 4 Trials Conducted with BEYFORTUS for the Prevention of MA RSV LRTI
Trial | Population | Study Arms
D5290C00003 (Trial 03) NCT02878330 | Infants born at ≥29 to <35 weeks GA entering their first RSV season | BEYFORTUS (N=969) [All subjects in Trial 03 were included in the efficacy analysis. All subjects in Trial 03 received 50 mg of BEYFORTUS IM injections regardless of body weight. The recommended BEYFORTUS dose in neonates and infants born during or entering their first RSV season is single IM 50 mg and 100 mg dose for those who weigh <5 kg and ≥5 kg, respectively [see Dosage and Administration (2.1)].] Placebo (N=484)
D5290C00004 (Trial 04) NCT03979313 | Infants born at ≥35 weeks GA entering their first RSV season | Primary Cohort [The primary efficacy analysis for Trial 04 is based on subjects from the Primary Cohort. For Trial 04 safety population [see Adverse Reactions (6.1)].] : BEYFORTUS (N=994) Placebo (N=496) Safety Cohort [Trial 04 safety analysis included both Primary and Safety Cohorts [see Adverse Reactions (6.1)].] : BEYFORTUS (N=1,015) Placebo (N=507)
D5290C00005 (Trial 05) NCT03959488 | Infants born at <35 weeks GA and infants born with CLD or CHD entering their first RSV season | RSV Season One: BEYFORTUS (N=616) Palivizumab (N=309)
 | Infants with CLD or CHD only entering their second RSV season | RSV Season Two: BEYFORTUS (N=220) Palivizumab (N=42)
VAS00006 (Trial 09) NCT05437510 | Infants born ≥29 weeks GA entering their first RSV season | BEYFORTUS (N=4,016) No intervention (N=4,018)
GA gestational age; CLD chronic lung disease; CHD hemodynamically significant chronic heart disease

14.2 Prevention of MA RSV LRTI in Infants Born at ≥29 to <35 Weeks Gestational Age (Trial 03)

Trial 03 was a randomized, double-blind, placebo-controlled multicenter trial for the prevention of Medically Attended Respiratory Syncytial Virus Lower Respiratory Tract Infection (MA RSV LRTI) conducted in preterm infants born at gestational age (GA) greater than or equal to 29 weeks and less than 35 weeks. These subjects were randomized 2:1 to receive BEYFORTUS (N=969) or placebo (N=484) by IM injection. All subjects in the BEYFORTUS arm received 50 mg IM of BEYFORTUS regardless of body weight. The recommended BEYFORTUS dose in neonates and infants born during or entering their first RSV season is a single IM 50 mg or 100 mg dose for those who weigh less than 5 kg and greater than or equal to 5 kg, respectively [see Dosage and Administration (2.1)].

At randomization, 20% were GA greater than or equal to 29 weeks and less than 32 weeks; 80% were GA greater than or equal to 32 and less than 35 weeks; 52% were male; 72% were White; 18% were Black; 1% were Asian; 1% were Pacific Islander, and 8% were Other or Mixed Race; 22% were Hispanic or Latino; 68% were from Northern Hemisphere. The median age was 2.8 months (range: 0.1 to 11.9 months); 53% were less than or equal to 3 months; 33% were greater than 3 to less than or equal to 6 months, and 14% were greater than 6 months of age.

The primary endpoint was the incidence of MA RSV LRTI caused by RT-PCR-confirmed RSV, characterized predominantly as bronchiolitis or pneumonia through 150 days after dosing. Medically Attended (MA) includes all healthcare provider visits such as physician office, urgent care, emergency room visits and hospitalizations. Signs of LRTI involvement included rhonchi, rales, crackles, or wheezing; and at least one sign of worsening clinical severity including at least one of the following: increased respiratory rate, hypoxemia, acute hypoxic or ventilatory failure, new onset apnea, nasal flaring, retractions, grunting, or dehydration due to respiratory distress. Incidence of RSV LRTI with hospitalization was a prespecified secondary endpoint. RSV hospitalization was defined as hospitalization for LRTI with a positive RSV test.

Table 5 displays the primary efficacy result for Trial 03.

Table 5 Incidence of MA RSV LRTI in Infants Born at ≥29 Weeks to <35 Weeks Through 150 Days Post Dose (Trial 03)
 | N | Incidence % (n) | Efficacy [Efficacy for MA RSV LRTI based on relative risk reduction against placebo adjusted for age at randomization and hemisphere.] (95% CI)
BEYFORTUS | 969 | 2.6% (25) | 70.1% (52.3, 81.2) [p-value =<0.001.] [In a post-hoc analysis of all randomized infants in Trial 03 weighing <5 kg at baseline, and who received the recommended dose of BEYFORTUS, efficacy for MA RSV LRTI, based on relative risk reduction against placebo was 86.2% (95% CI 68.0, 94.0); efficacy for RSV LRTI with hospitalization based on relative risk reduction against placebo was 86.5% (95% CI 53.5, 96.1).]
Placebo | 484 | 9.5% (46) | 70.1% (52.3, 81.2) [p-value =<0.001.] [In a post-hoc analysis of all randomized infants in Trial 03 weighing <5 kg at baseline, and who received the recommended dose of BEYFORTUS, efficacy for MA RSV LRTI, based on relative risk reduction against placebo was 86.2% (95% CI 68.0, 94.0); efficacy for RSV LRTI with hospitalization based on relative risk reduction against placebo was 86.5% (95% CI 53.5, 96.1).]

In Trial 03, the efficacy of BEYFORTUS against MA RSV LRTI with hospitalization in infants born at GA greater than or equal to 29 weeks and less than 35 weeks, who received a single dose of 50 mg BEYFORTUS, based on the relative risk reduction was 78.4% (95% CI 51.9, 90.3; p=0.0002), through 150 days post dose.

14.3 Prevention of MA RSV LRTI in Infants Born at ≥35 Weeks Gestational Age (Trial 04)

BEYFORTUS was evaluated in one Phase 3 randomized, double-blind, placebo-controlled multicenter trial, Trial 04, for the prevention of MA RSV LRTI in term and late preterm infants GA greater than or equal to 35 weeks entering their first RSV season.

The primary analysis population (Primary Cohort) included 1,490 term and late preterm infants (GA greater than or equal to 35 weeks). Subjects were randomized 2:1 to receive a single IM dose of BEYFORTUS (N=994) (50 mg if less than 5 kg body weight or 100 mg if greater than or equal to 5 kg body weight at the time of dosing), or placebo (N=496). At randomization, 14% were GA greater than or equal to 35 weeks and less than 37 weeks; 86% were GA greater than or equal to 37 weeks; 52% were male; 53% were White; 28% were Black; 6% were American Indian/Alaskan native; 4% were Asian; 1% were Pacific Islander; and 8% were Other or Mixed Race; 10% were Hispanic or Latino; 69% were from Northern Hemisphere; and 40% weighed less than 5 kg. The median age was 2.6 months (range: 0.03 to 11.10 months); 58% were less than or equal to 3 months; 32% were greater than 3 to less than or equal to 6 months, and 10% were greater than 6 months of age.

In Trial 04, the primary endpoint was the incidence of MA RSV LRTI caused by RT-PCR-confirmed RSV, as defined in Trial 03. Incidence of RSV LRTI with hospitalization was a prespecified secondary endpoint. RSV hospitalization was defined as hospitalization for LRTI with a positive RSV test.

Table 6 displays the primary efficacy result from Trial 04.

Table 6 Incidence of MA RSV LRTI in Infants Born at ≥35 Weeks Through 150 Days Post Dose (Trial 04) [The primary efficacy analysis for Trial 04 is based on subjects from the Primary Cohort.]
 | N | Incidence % (n) | Efficacy [Efficacy for MA RSV LRTI based on relative risk reduction against placebo adjusted for age at randomization.] (95% CI)
BEYFORTUS | 994 | 1.2% (12) | 74.9% (50.6, 87.3) [p-value =<0.001.]
Placebo | 496 | 5.0% (25) | 74.9% (50.6, 87.3) [p-value =<0.001.]

In Trial 04, the efficacy of BEYFORTUS against MA RSV LRTI with hospitalization in infants born at GA greater than or equal to 35 weeks, who received a single IM 50 mg or 100 mg dose for those who weigh less than 5 kg and greater than or equal to 5 kg, respectively, based on the relative risk reduction was 60.2% (95% CI -14.6, 86.2; p=0.09), through 150 days post dose.

14.4 Prevention of MA RSV LRTI in Infants Born at <35 Weeks Gestational Age and Infants with CLD of Prematurity or Hemodynamically Significant CHD (Trial 05)

The safety and PK of BEYFORTUS were evaluated in a Phase 2/3 randomized, double-blind, palivizumab-controlled multicenter trial (Trial 05) in pediatric subjects born less than 35 weeks GA and infants with CLD of prematurity or hemodynamically significant CHD. This trial was not powered for efficacy, but efficacy was assessed as secondary endpoint. The efficacy of BEYFORTUS in preterm infants (GA less than 35 weeks) during their first RSV season and in pediatric subjects up to 24 months of age with CLD or CHD during their first and second RSV season was established by extrapolation of efficacy of BEYFORTUS from Trials 03 and Trial 04 to the population enrolled in Trial 05 based on similar nirsevimab-alip exposures among subjects enrolled in Trial 04 and 05 [see Clinical Pharmacology (12.3)].

Trial 05: RSV Season One

Trial 05 enrolled infants at higher risk for severe RSV disease entering their first RSV season into one of two cohorts: preterm infants (GA less than 35 weeks) and infants with CLD of prematurity or hemodynamically significant CHD. A total of 925 infants were randomized 2:1 in each of the preterm (n=615) and CLD/CHD (n=310) cohorts to receive BEYFORTUS or palivizumab. Infants received a single IM dose of BEYFORTUS (50 mg if less than 5 kg body weight or 100 mg if greater than 5 kg body weight at the time of dosing), followed by 4 once-monthly IM doses of placebo, or 5 once-monthly IM doses of 15 mg/kg palivizumab, respectively. At randomization, in the preterm cohort, 77 infants (13%) were less than 29 weeks GA; and 499 (81%) were GA greater than or equal to 29 to less than 35 weeks. In the CLD/CHD cohort, 70% had CLD of prematurity; 34% had hemodynamically significant CHD; 123 infants (40%) were less than 29 weeks GA, 28% were greater than or equal to 29 weeks to less than 35 weeks GA; and 32% were greater than or equal to 35 weeks GA. In both cohorts together, 54% were male; 79% were White; 10% were Black; 5% were Asian; 2% were American Indian/Alaskan Native; 15% were Hispanic or Latino; and 57% weighed less than 5 kg. The median age was 3.5 months (range: 0.07 to 12.3 months); 45% were less than or equal to 3 months; 34% were greater than 3 months to less than or equal to 6 months, and 21% were greater than 6 months of age.

In the first RSV season of Trial 05, the incidence of MA RSV LRTI through 150 days post dose was 0.6% (4/616) in the BEYFORTUS group and 1.0% (3/309) in the palivizumab group.

Trial 05: RSV Season Two

Pediatric subjects with CLD of prematurity or hemodynamically significant CHD up to 24 months of age continued in the trial for a second RSV season (n=262). Subjects who received BEYFORTUS during their first RSV season also received a single dose of 200 mg BEYFORTUS entering their second RSV season followed by 4 once-monthly IM doses of placebo (n=180). Subjects who received palivizumab during their first RSV season were re-randomized 1:1 to either receive BEYFORTUS or palivizumab entering their second RSV season. Forty subjects who received palivizumab in the first RSV season received a single IM dose of BEYFORTUS followed by 4 once-monthly IM doses of placebo in their second RSV season; and 42 subjects received palivizumab (5 once-monthly IM doses of 15 mg/kg palivizumab) in both first and second RSV seasons.

In the second RSV season of Trial 05, there were no cases of MA RSV LRTI through Day 150 post-dose in subjects who received either BEYFORTUS or palivizumab.

14.5 Prevention of RSV LRTI Hospitalization in Term and Preterm Infants (Trial 09)

Trial 09 is a Phase 3b, randomized open-label trial consisting of 8,058 term and preterm infants (GA greater than or equal to 29 weeks) born during or entering their first RSV season who received either a single IM dose of BEYFORTUS (50 mg if less than 5 kg body weight or 100 mg if greater than or equal to 5 kg body weight at the time of dosing) or no intervention. The trial was conducted under real world conditions in the United Kingdom (51% of subjects), France (27%), and Germany (22%). At randomization, the median age was 4 months (range: 0 to 12 months); 49% of infants were less than or equal to 3 months; 24% were greater than 3 to less than or equal to 6 months, and 28% were greater than 6 months of age. Of these infants, 52% were male and 48% were female. Most subjects were term infants, with a gestational age at birth of greater than or equal to 37 weeks (85%). Half of the subjects were born during the RSV season. The majority of subjects (99%) in the BEYFORTUS group received their BEYFORTUS dose during the RSV season.

The primary endpoint for Trial 09 was the overall incidence of RSV LRTI hospitalization caused by confirmed RSV infection, through the RSV season. Subjects were followed through the end of the RSV season for efficacy and through Day 365 for safety. The median efficacy follow-up time from intervention or randomization to the end of the RSV season was 2.3 months (range: 0 to 7.0 months) in the BEYFORTUS group and 2.0 months (range: 0 to 6.8 months) in the no intervention group. RSV LRTI hospitalizations occurred in 11 of 4,037 infants in the BEYFORTUS group (incidence rate=0.001) and in 60 of 4,021 infants in the no intervention group (incidence rate=0.006) through the RSV season, for an efficacy based on relative risk reduction of 83.2% (95% CI 67.8, 92.0).

16 HOW SUPPLIED/STORAGE AND HANDLING

How Supplied

BEYFORTUS injection is a sterile, preservative-free, clear to opalescent, colorless to yellow solution supplied as follows:

- One 50 mg/0.5 mL single-dose pre-filled syringe in a carton: NDC 49281-575-00
- Five 50 mg/0.5 mL single-dose pre-filled syringes in a carton: NDC 49281-575-15
- One 100 mg/mL single-dose pre-filled syringe in a carton: NDC 49281-574-88
- Five 100 mg/mL single-dose pre-filled syringes in a carton: NDC 49281-574-15

Each BEYFORTUS pre-filled syringe is for one time use only.

Storage and Handling

Store refrigerated between 36°F to 46°F (2°C to 8°C). BEYFORTUS may be kept at room temperature 68°F to 77°F (20°C to 25°C) for a maximum of 8 hours. After removal from the refrigerator, BEYFORTUS must be used within 8 hours or discarded.

Store BEYFORTUS in original carton to protect from light until time of use.

Do not freeze. Do not shake. Do not expose to heat.

17 PATIENT COUNSELING INFORMATION

Advise the child's caregiver to read the FDA-approved patient labeling (Patient Information).

Hypersensitivity Reactions Including Anaphylaxis

Inform the patient's caregiver of the signs and symptoms of potential hypersensitivity reactions, and advise the caregiver to seek medical attention immediately if the child experiences a hypersensitivity reaction to BEYFORTUS [see Warnings and Precautions (5.1)].

Dosage and Administration

Advise the caregiver that the child will receive one dose of BEYFORTUS by IM injection by a healthcare provider. If the child remains at increased risk for RSV, they may receive a second dose in the second RSV season [see Dosage and Administration (2.1)].

Manufactured by: Sanofi Pasteur Inc. Swiftwater, PA 18370 USA

US License No. 1725

At: AstraZeneca Pharmaceuticals LP, Frederick, MD 21703 USA

For patent information: https://www.sanofi.us/en/products-and-resources/patents

BEYFORTUS is a registered trademark of the Sanofi group of companies.

PATIENT INFORMATION
BEYFORTUS® (Bay for tus)
(nirsevimab-alip)
injection, for intramuscular use

What is BEYFORTUS?
BEYFORTUS is a prescription medicine that is used to help prevent a serious lung disease caused by Respiratory Syncytial Virus (RSV) in:

- newborns and babies under 1 year of age born during or entering their first RSV season.
- children up to 24 months of age who remain at risk of severe RSV disease through their second RSV season.

BEYFORTUS is an antibody that contains nirsevimab-alip which is used to help prevent RSV disease for 5 months.
It is not known if BEYFORTUS is safe and effective in children older than 24 months of age.

Your child should not receive BEYFORTUS if your child has a history of serious allergic reactions to nirsevimab-alip or any of the ingredients in BEYFORTUS. See the end of this Patient Information leaflet for a complete list of ingredients in BEYFORTUS.

Before your child receives BEYFORTUS, tell your healthcare provider about all of your child's medical conditions, including if your child:

- has ever had a reaction to BEYFORTUS.
- has bleeding or bruising problems. If your child has a problem with bleeding or bruises easily, an injection could cause a problem.

Tell your child's healthcare provider about all the medicines your child takes, including prescription and over-the-counter medicines, vitamins, and herbal supplements. Your infant should not receive a medicine called palivizumab if they have already received BEYFORTUS in the same RSV season.

How is BEYFORTUS given?

- BEYFORTUS is given as an injection, usually in the thigh (leg) muscle, by your child's healthcare provider.
- Your child should receive BEYFORTUS before or during the RSV season. RSV season is the time of year when RSV infections are most common, usually occurring fall through spring. Your healthcare provider can tell you when the RSV season starts in your area.
- Your child may still get RSV disease after receiving BEYFORTUS. Talk to your child's healthcare provider about what symptoms to look for.
- If your child has heart surgery, your child's healthcare provider may need to give your child an additional BEYFORTUS injection soon after surgery.

What are the possible side effects of BEYFORTUS?

- Serious allergic reactions have happened with BEYFORTUS.
- Get medical help right away if your child has any of the following signs or symptoms of a serious allergic reaction:

- swelling of the face, mouth, or tongue
- difficulty swallowing or breathing
- unresponsiveness

- bluish color of skin, lips or under fingernails
- muscle weakness
- severe rash, hives or itching

The most common side effects of BEYFORTUS include rash, and pain, swelling or hardness at the site of your child's injection.
These are not all of the possible side effects of BEYFORTUS.
Call your doctor for medical advice about side effects. You may report side effects to FDA at 1-800-FDA-1088.

General information about the safe and effective use of BEYFORTUS.
Medicines are sometimes prescribed for purposes other than those listed in a Patient Information leaflet. You can ask your pharmacist or healthcare provider for information about BEYFORTUS that is written for health professionals.

What are the ingredients in BEYFORTUS?
Active ingredient: nirsevimab-alip
Inactive ingredients: arginine hydrochloride, histidine, L-histidine hydrochloride monohydrate, polysorbate 80, sucrose and water for injection.
Manufactured by: Sanofi Pasteur Inc. Swiftwater, PA 18370 USA
US License No. 1725
At: AstraZeneca Pharmaceuticals LP, Frederick, MD 21703 USA
BEYFORTUS is a registered trademark of the Sanofi group of companies.
For more information, go to https://www.Beyfortus.com or call 1-855-239-3678 (1-855-BEYFORTUS).

This Patient Information has been approved by the U.S. Food and Drug Administration.

Revised: October 2025

PRINCIPAL DISPLAY PANEL - 0.5 mL Syringe Carton

NDC 49281-575-15

Rx only

Beyfortus®
(nirsevimab-alip)
Injection

50 mg / 0.5 mL

For Intramuscular Injection Only

Store the pre-filled syringe in original carton to protect from light until time of use.

Must be administered by a healthcare provider.

Five 0.5 mL single-dose prefilled syringes

sanofi

PRINCIPAL DISPLAY PANEL - 1 mL Syringe Carton

NDC 49281-574-15

Rx only

Beyfortus®
(nirsevimab-alip)
Injection

100 mg/mL

For Intramuscular Injection Only

Store the pre-filled syringe in original carton to protect from light until time of use.

Must be administered by a healthcare provider.

Five 1 mL single-dose prefilled syringes

sanofi